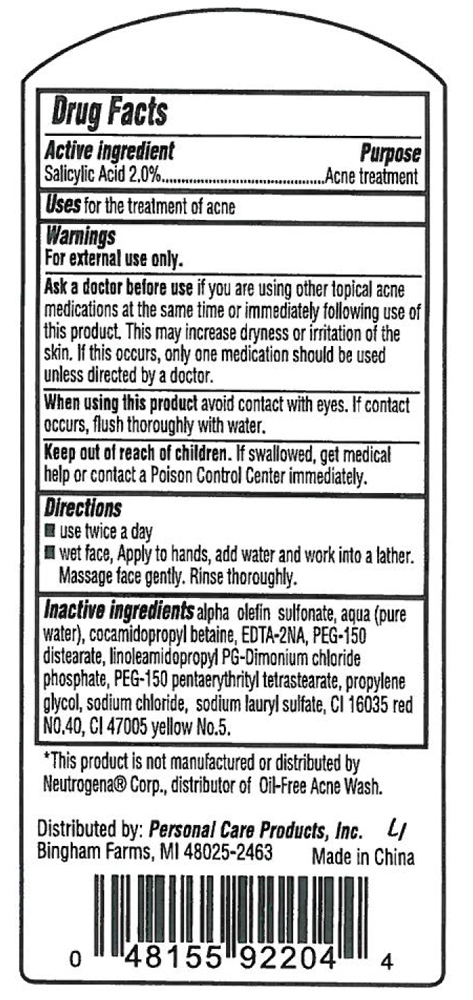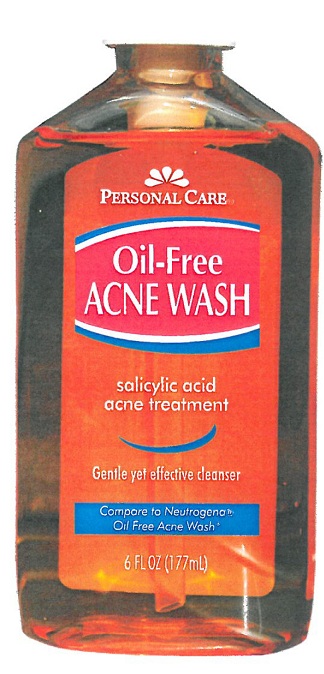 DRUG LABEL: Oil Free Acne Wash
                        
NDC: 29500-0177 | Form: LIQUID
Manufacturer: Personal Care Products, Inc.
Category: otc | Type: HUMAN OTC DRUG LABEL
Date: 20111230

ACTIVE INGREDIENTS: SALICYLIC ACID 2 mL/100 mL
INACTIVE INGREDIENTS: WATER; COCAMIDOPROPYL BETAINE; EDETATE SODIUM; PROPYLENE GLYCOL; SODIUM CHLORIDE; SODIUM LAURYL SULFATE

Personal Care Oil Free Acne Wash

Active Ingredient Purpose

Salicylic Acid.............................................Acne Treatment

PURPOSE

Uses: for the treatment of acne

Warnings for external use only.

Ask a doctor before use if you are using other topical acne medications t the same time or immediately following use of this product. This may increase dryness or irritation of the skin. If this occurs, only one medication should be used unless directed by a doctor.

INDICATIONS AND USAGE

Uses for the treatment of acne

Keep out of reach of children. If swallowed, get medical help or contact a Poison Control Center immediately.

DOSAGE AND ADMINISTRATION

Directions use twice a day

wet face, apply to hands, add water and work into a lather. Massage face gently. Rinse thoroughly.

INACTIVE INGREDIENT

alpha olefin sulfonate, aqua (pure water), cocamidopropyl betaine, EDTA-2NA, PEG-150 distearate, linoleamidopropyl PG-Dimonium chloride phosphate, PEG 150 penterythrityl tetrastearate, propylene glycol, sodium chloride, sodium lauryl sulfate, CI 16035 red NO 40, CI47005 yellow No. 5

*This product is not manufactured or distributed by Neutrogena Corp distributor of Oil Free Acne Wash

Distributed by: Personal Care Products, Inc.

Bingham Farms, MI 48025-2463 Made in China

PACKAGE LABEL

Personal Care

Oil Free Acne Wash

Salicylic Acid

Acne Treatment

Gentle yet effective cleanser

Compare to Neutrogena

Oil Free Acne Wash

6FL OZ (177 ML)